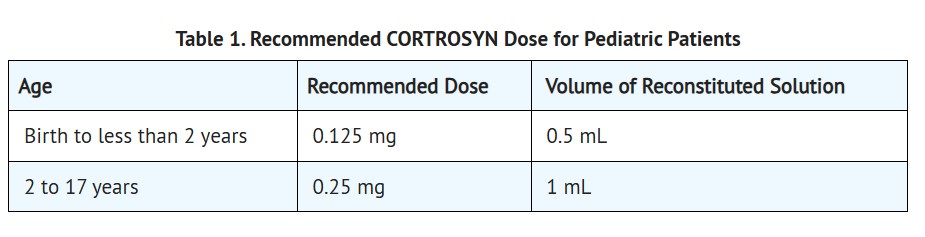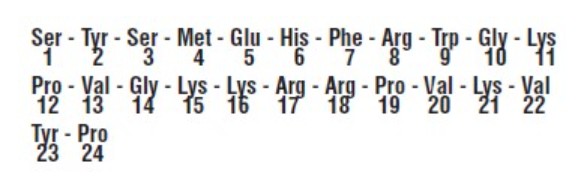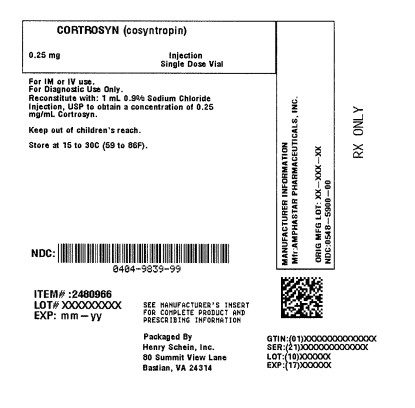 DRUG LABEL: Cortrosyn
NDC: 0404-9839 | Form: INJECTION, POWDER, LYOPHILIZED, FOR SOLUTION
Manufacturer: Henry Schein, Inc.
Category: prescription | Type: HUMAN PRESCRIPTION DRUG LABEL
Date: 20250617

ACTIVE INGREDIENTS: Cosyntropin 0.25 mg/1 mL

HIGHLIGHTS OF PRESCRIBING INFORMATION

These highlights do not include all the information needed to use CORTROSYN® safely and effectively.
See full prescribing information for CORTROSYN®.
CORTROSYN (cosyntropin) for injection, for intravenous or intramuscular use
Initial U.S. Approval: 2008

1 Indications and Usage

CORTROSYN is an adrenocorticotropin hormone indicated, in combination with other diagnostic tests, for use as a diagnostic agent in the screening of adrenocortical insufficiency in adults and pediatric patients. (1)

2 Dosage and Administration

- In general, stop glucocorticoids and spironolactone on the day of CORTROSYN testing. For long-acting glucocorticoids, stop for a longer period before CORTROSYN testing. (2.1)
- For adults, the recommended dose is 0.25 mg to be administered by intravenous or intramuscular injection. (2.2)
- For pediatric patients, the recommended dose to be administered by intravenous or intramuscular injection is (2.3):

◦ 0.125 mg for patients birth to less than 2 years of age

◦ 0.25 mg for patients 2 to 17 years of age

- Obtain blood samples for serum cortisol level at baseline and exactly 30 and 60 minutes after CORTROSYN administration. (2.5)
- See Full Prescribing Information for reconstitution and interpretation of cortisol levels information. (2.4, 2.6)

3 Dosage Forms and Strengths

- For injection: 0.25 mg of cosyntropin as a lyophilized powder in single-dose vial for reconstitution (3)

4 Contraindications

- CORTROSYN is contraindicated in patients with a history of hypersensitivity to cosyntropin or to any excipients of CORTROSYN. Reactions have included anaphylaxis. (4, 5.1)

5 Warnings and Precautions

- Hypersensitivity: reactions including anaphylaxis have been reported. Monitor patients for hypersensitivity reactions and treat as needed. (5.1)
- Diagnostic Inaccuracies: Cortisol levels and subsequent diagnosis of adrenocortical insufficiency following CORTROSYN administration may be inaccurate if patients are on certain medications because of their effect on cortisol or cortisol binding globulin levels. Any condition that elevates or lowers cortisol binding globulin levels may increase or decrease plasma total cortisol levels, respectively. (2.1, 5.2, 7)

6 Adverse Reactions

Most common adverse reactions are: anaphylactic reaction, bradycardia, tachycardia, hypertension, peripheral edema, and rash (6)

To report SUSPECTED ADVERSE REACTIONS, contact Amphastar Pharmaceuticals, Inc. at 1-800-423-4136 or FDA at 1-800-FDA-1088 or www.fda.gov/medwatch.

7 Drug Interactions

- Drug effects on plasma cortisol levels:

◦ Accuracy of the test results can be affected by concomitant medications.◦ Glucocorticoids and spironolactone: May falsely elevate plasma cortisol levels. Stop these drugs on day of CORTROSYN testing. Long-acting glucocorticoids may need to be stopped for a longer period before CORTROSYN testing. (7)◦ Estrogen: May elevate plasma total cortisol levels. Stop estrogen containing drugs 4 to 6 weeks before CORTROSYN testing. (7)

See 17 for PATIENT COUNSELING INFORMATION

Revised 12/2023

FULL PRESCRIBING INFORMATION

Highlights of Prescribing Information

These highlights do not include all the information needed to use CORTROSYN® safely and effectively.
See full prescribing information for CORTROSYN®.
CORTROSYN (cosyntropin) for injection, for intravenous or intramuscular use
Initial U.S. Approval: 2008

1 Indications and Usage

CORTROSYN is indicated, in combination with other diagnostic tests, for use as a diagnostic agent in the screening of adrenocortical insufficiency in adults and pediatric patients.

2 Dosage and Administration

2.1 Important Information Before Conducting

CORTROSYN TESTING

- In general, stop glucocorticoids and spironolactone on the day of CORTROSYN testing. However, long-acting glucocorticoids may need to be stopped for a longer period before CORTROSYN testing [see Warnings and Precautions (5.2), Drug Interactions (7)].
- Stop estrogen-containing drugs four to six weeks before CORTROSYN testing [see Warnings and Precautions (5.2), Drug Interactions (7)].

2.2 Recommended Dose for Adults

- The recommended dose of CORTROSYN in adults is 0.25 mg to be administered by intravenous or intramuscular injection.

2.3 Recommended Dose for Pediatric Patients

- The recommended dose of CORTROSYN in pediatric patients, aged birth to 17 years, to be administered by intravenous or intramuscular injection is presented in Table 1.

2.4 Reconstitution Instructions

- Aseptically reconstitute the lyophilized powder in the vial using 1 mL of 0.9% Sodium Chloride Injection, USP and gently swirl.
- After reconstitution, the final concentration of CORTROSYN reconstituted solution is 0.25 mg/mL.
- Parenteral drug products should be inspected visually for particulate matter and discoloration prior to administration, whenever solution and container permit. The reconstituted CORTROSYN solution should be clear and colorless, and free of particulates. If CORTROSYN solution is cloudy or contains particulates, do not administer.
- If the CORTROSYN reconstituted solution is not used immediately, discard the unused CORTROSYN reconstituted solution.

2.5 Administration Information

CORTROSYN may be administered by intramuscular or intravenous injection.
Obtain blood sample for baseline serum cortisol. Obtain blood samples again for assessment of cortisol levels exactly 30 minutes and 60 minutes after administration of CORTROSYN.

2.6 Interpretation of Plasma Cortisol Levels after CORTROSYN Injection

Stimulated plasma cortisol levels of less than 18 mcg/dL at 30- or 60-minutes post CORTROSYN injection are suggestive of adrenocortical insufficiency. Cutoff values for exclusion of adrenocortical insufficiency may vary according to the assay used. Test results can be affected by concomitant medications and certain medical conditions [see Warnings and Precautions (5.2)].

3 Dosage Forms and Strengths

For Injection: 0.25 mg of cosyntropin as a lyophilized powder in a single-dose vial for reconstitution.

4 Contraindications

CORTROSYN is contraindicated in patients with a history of hypersensitivity to cosyntropin or to any excipients of CORTROSYN. Reactions have included anaphylaxis [see Warnings and Precautions (5.1)].

5 Warnings and Precautions

5.1 Hypersensitivity to CORTROSYN Injection

CORTROSYN injection hypersensitivity reactions including anaphylaxis have been reported. Monitor patients for hypersensitivity reactions and treat as needed.

5.2 Diagnostic Inaccuracies

Cortisol levels and subsequent diagnosis of adrenocortical insufficiency following CORTROSYN administration may be inaccurate if patients are on certain medications because of their effect on cortisol or cortisol binding globulin levels.

Glucocorticoids and spironolactone may result in falsely elevated cortisol levels. Stop these drugs on the day of CORTROSYN testing. Long-acting glucocorticoids may need to be stopped for a longer period before CORTROSYN testing [see Dosage and Administration (2.1) and Drug Interactions (7)].

Estrogen-containing drugs increase cortisol binding globulin levels which can increase plasma total cortisol levels. To obtain accurate plasma total cortisol levels, stop estrogen containing drugs four to six weeks before CORTROSYN testing to allow cortisol binding globulin levels to return to levels within the reference range [see Dosage and Administration (2.1) and Drug Interactions (7)]. Alternatively, concomitant measurement of cortisol binding globulin at the time of testing can be done; if cortisol binding globulin levels are elevated, plasma total cortisol levels are considered inaccurate.

Any condition that elevates or lowers cortisol binding globulin levels may increase or decrease plasma total cortisol levels, respectively. Cortisol binding globulin levels can be low in cirrhosis or nephrotic syndrome. Measure cortisol binding globulin levels as necessary to ensure accuracy of interpretation of plasma total cortisol levels.

6 Adverse Reactions

Because adverse reactions are reported voluntarily from a population of uncertain size, it is not always possible to reliably estimate their frequency or establish a causal relationship to drug exposure. The following adverse reactions have been identified during post approval use of CORTROSYN:

- anaphylactic reaction
- bradycardia
- tachycardia
- hypertension
- peripheral edema
- rash

7 Drug Interactions

7.1 Drug Effects on Plasma Cortisol Levels

- Accuracy of the test results can be affected by concomitant medications. Plasma cortisol levels and subsequent diagnosis of adrenocortical insufficiency following CORTROSYN administration may be inaccurate if patients are on certain medications because of their effect on cortisol or cortisol binding globulin levels [see Dosage and Administration (2.1) and Warnings and Precautions (5.2)].
- Glucocorticoids and spironolactone: May falsely elevate plasma cortisol levels. Stop these drugs on the day of CORTROSYN testing. Long-acting glucocorticoids may need to be stopped for a longer period before CORTROSYN testing.
- Estrogen: May elevate plasma total cortisol levels. Stop estrogen containing drugs 4 to 6 weeks before CORTROSYN testing to allow cortisol binding globulin levels to return to levels within the reference range. Alternatively, concomitant measurement of cortisol binding globulin at the time of testing can be done; if cortisol binding globulin levels are elevated, plasma total cortisol levels are considered inaccurate.

8 Use in Specific Populations

8.1 Pregnancy
Risk Summary
Available data from case reports over decades of use with cosyntropin during pregnancy have not identified an increased risk of major birth defects, miscarriage or adverse maternal or fetal outcomes. Unidentified adrenal insufficiency can result in adverse maternal or fetal outcomes (see Clinical Considerations).

The background risk of major birth defects and miscarriage for the indicated population is unknown. All pregnancies have a background risk of birth defect, loss, or other adverse outcomes. In the U.S. general population, the estimated background risk for major birth defects and miscarriage in clinically recognized pregnancies is 2% to 4% and 15% to 20%, respectively.

Clinical Considerations
Disease-associated maternal and/or embryo/fetal risk Unidentified adrenal insufficiency during pregnancy can result in maternal and/or fetal death; therefore, the diagnosis of suspected adrenal insufficiency during pregnancy should not be delayed.

8.2 Lactation
Risk Summary
There are no data on the presence of cosyntropin in human milk, the effects on the breastfed infant, or the effects on milk production. The developmental and health benefits of breastfeeding should be considered along with the mother’s clinical need for CORTROSYN and any potential adverse effects on the breastfed infant from CORTROSYN or from the underlying maternal condition.

8.4 Pediatric Use
CORTROSYN is approved for use in pediatric patients [see Dosage and Administration (2.3)].

11 Description

Cosyntropin is an adrenocorticotropic hormone (ACTH). Cosyntropin is synthetic beta 1 - 24 corticotropin, a synthetic subunit of ACTH. It is an open chain polypeptide containing, the first 24 of the 39 amino acids of natural ACTH in sequence from N terminal. The sequence of amino acids in the 1 - 24 compound is as follows:

The empirical formula is C136H210N40O31S with a molecular weight of 2934 g/mol.

CORTROSYN (cosyntropin) for Injection is a sterile lyophilized powder in single-dose vials containing 0.25 mg of cosyntropin and 10 mg of mannitol. Sodium Hydroxide and Glacial acetic acid may be used to adjust pH.

12 Clinical Pharmacology

12.1 Mechanism of Action
Cosyntropin exhibits the full corticosteroidogenic activity of natural ACTH. Various studies have shown that the biologic activity of ACTH resides in the N-terminal portion of the molecule and that the 1-20 amino acid residue is the minimal sequence retaining full activity. Partial or complete loss of activity is noted with progressive shortening of the chain beyond 20 amino acid residues. For example, the decrement from 20 to 19 results in a 70% loss of potency.

The pharmacologic profile of CORTROSYN is similar to that of purified natural ACTH. It has been established that 0.25 mg of CORTROSYN will stimulate the adrenal cortex maximally and to the same extent as 25 units of natural ACTH. This dose of CORTROSYN will produce maximal secretion of 17-OH corticosteroids, 17-ketosteroids and/or 17-ketogenic steroids.

12.2 Pharmacodynamics
Animal, human and synthetic ACTH (1-39) which all contain 39 amino acids exhibit similar immunologic activity. This activity resides in the C-terminal portion of the molecule and the 22-39 amino acid residues exhibit the greatest degree of antigenicity. In contrast, synthetic polypeptides containing 1-19 or fewer amino acids have no detectable immunologic activity. Those containing 1-26, 1-24 or 1-23 amino acids have very little immunologic although full biologic activity. This property of CORTROSYN assumes added importance in view of the known antigenicity of natural ACTH.

13 Nonclinical Toxicology

13.1 Carcinogenesis, Mutagenesis, Impairment of Fertility
Long-term carcinogenicity studies in animals to evaluate the carcinogenic potential of cosyntropin have not been conducted. Studies to evaluate mutagenic potential or impairment of fertility in animals have not been conducted.

16 How Supplied/Storage and Handling

How Supplied
CORTROSYN (cosyntropin) for injection 0.25 mg, in a single-dose vial for reconstitution.

Box contains 10 single-dose vials NDC 0548-5900-00

Storage and Handling
Store at 20º to 25ºC (68º to 77ºF); excursions permitted between 15° to 30°C (59° to 86°F) [see USP Controlled Room Temperature].

CORTROSYN injection is intended as a single-dose injection and contains no antimicrobial preservative. Any unused portion should be discarded.

Product repackaged by: Henry Schein, Inc., Bastian, VA 24314
From Original Manufacturer/Distributor's NDC and Unit of Sale | To Henry Schein Repackaged Product NDC and Unit of Sale | Total Strength/Total Volume (Concentration) per unit
NDC 0548-5900-00 Box of 10 vials | NDC 0404-9839-99 1 Vial in a bag (Vial bears NDC 0548-5900-00) | 0.25 mg

17 Patient Counseling Information

Advise the patient and/or caregiver to read the FDA-approved patient labeling (Patient Information).

Hypersensitivity Reactions, Including Anaphylaxis
Inform patients and/or caregivers of the early signs of hypersensitivity reactions including rash, hives, itching, facial swelling, tightness of the chest, and wheezing [see Contraindications (4), Warnings and Precautions (5.1)].

Drug Interference with CORTROSYN Testing
Advise patients and/or caregivers to stop taking glucocorticoids and spironolactone on the day of CORTROSYN testing. However, for patients taking long-acting glucocorticoids, advise them to stop for longer periods before CORTROSYN testing. Advise patients to stop taking estrogen-containing drugs four to six weeks before CORTROSYN testing [see Dosage and Administration (2.1), Warnings and Precautions (5.2), and Drug Interactions (7)].

Manufactured by:
Amphastar Pharmaceuticals, Inc.
Rancho Cucamonga, CA 91730 U.S.A.
Rev. 12-23